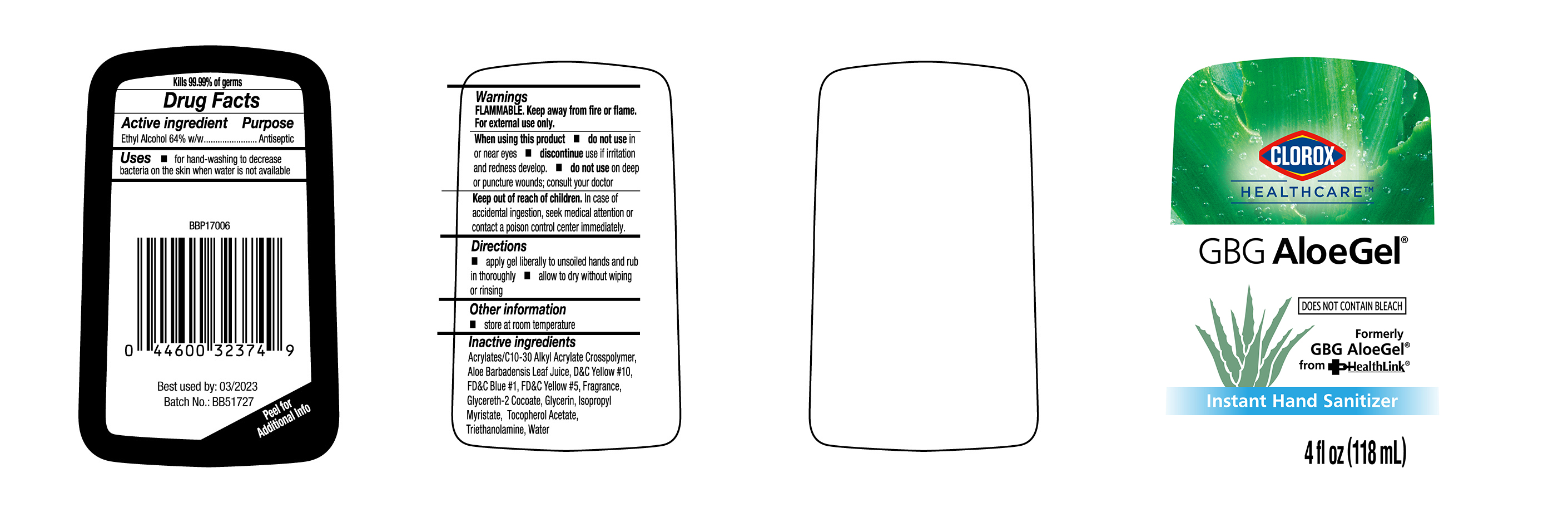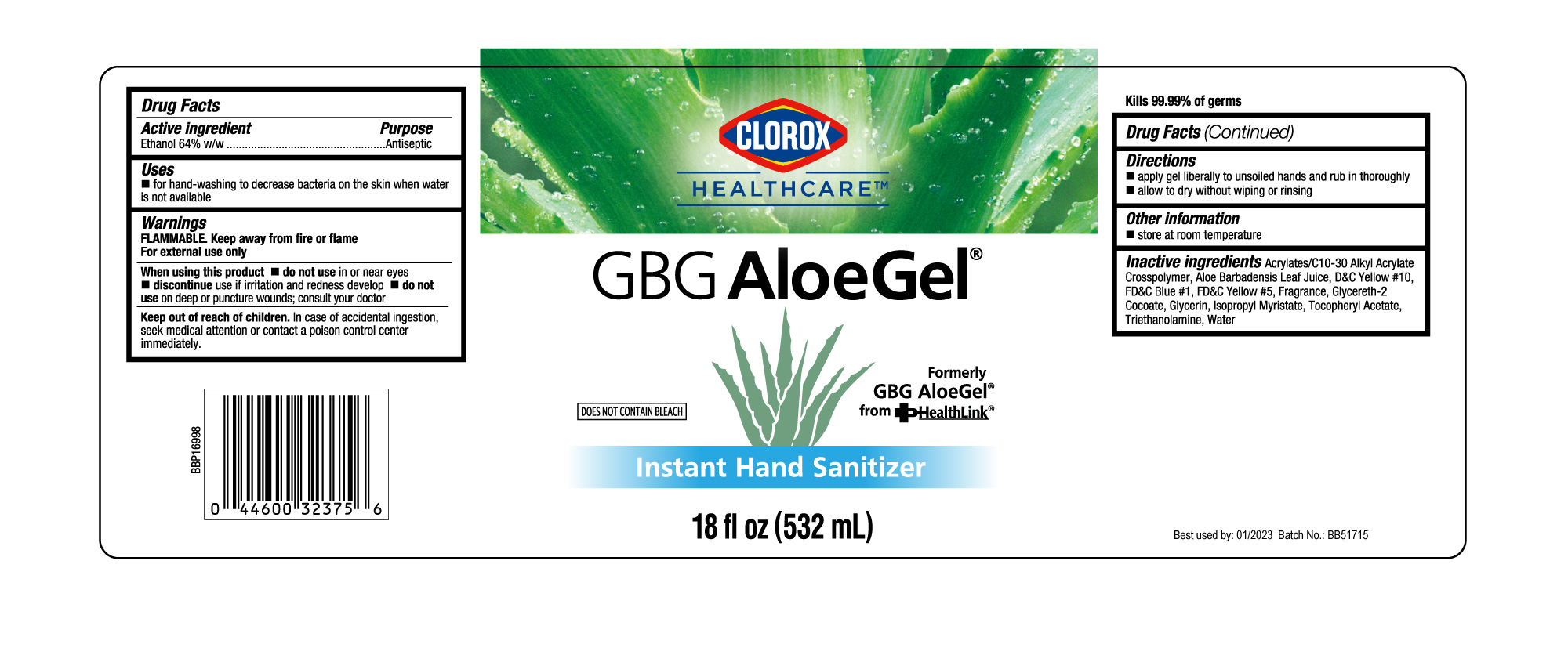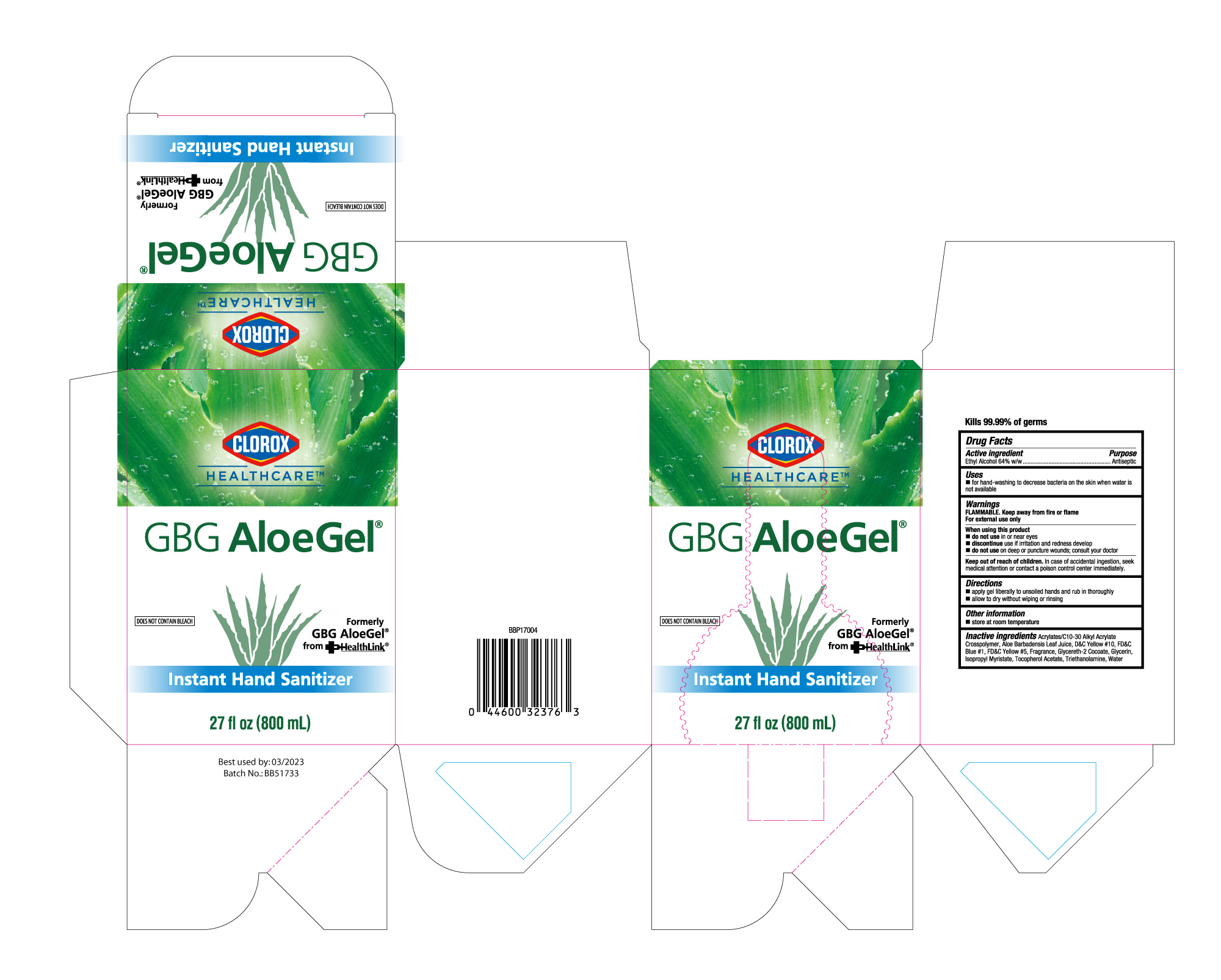 DRUG LABEL: HAND SANITIZER
NDC: 47993-327 | Form: GEL
Manufacturer: NINGBO JIANGBEI OCEAN STAR TRADING CO.,LTD
Category: otc | Type: HUMAN OTC DRUG LABEL
Date: 20210617

ACTIVE INGREDIENTS: ALCOHOL 64 g/112 mL
INACTIVE INGREDIENTS: CARBOMER INTERPOLYMER TYPE A (ALLYL SUCROSE CROSSLINKED); ALOE VERA LEAF; D&C YELLOW NO. 10; FD&C BLUE NO. 1; FD&C YELLOW NO. 5; GLYCERETH-2 COCOATE; GLYCERIN; ISOPROPYL MYRISTATE; .ALPHA.-TOCOPHEROL ACETATE; TROLAMINE; WATER

47993-327

Active ingredients

Ethanol 64% w/w

PURPOSE

Antiseptic

Uses：

- for hand-washing to decrease bacteria on the skin when water is not available.

Warnings:

FLAMMABLE. Keep away from fire or flame

For external use only.

When using this product

- do not use in or near eyes
- do not use on deep or puncture wounds; consult your doctor

- discotinue use if irritation and redness develop.

Keep out of reach of children. In case of accidental ingestion, seek medical attention or contact a poison control center immediately.

Directions:

- apply gel liberally to unsoiled hands and rub in thoroughly.
- allow to dry without wiping or rinsing.

Other information:

- store at room temperature.

Inactive ingredients:

Acrylates/C10-30 Alkyl Acrylate Crosspolymer, Aloe Barbadensis Leaf Juice, D&C Yellow #10, FD&C Blue #1, FD&C Yellow #5, Fragrance, Glycereth-2 Cocoate, Glycerin, Isopropyl Myristate, Tocopheryl Acetate, Triethanolamine, Water